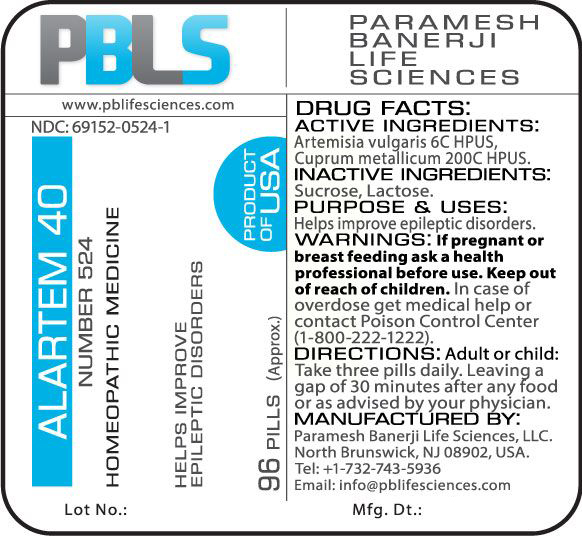 DRUG LABEL: Alartem 40 (Number 524)
NDC: 69152-0524 | Form: PELLET
Manufacturer: Paramesh Banerji Life Sciences LLC
Category: homeopathic | Type: HUMAN OTC DRUG LABEL
Date: 20170601

ACTIVE INGREDIENTS: ARTEMISIA VULGARIS ROOT 6 [hp_C]/1 1; COPPER 200 [hp_C]/1 1
INACTIVE INGREDIENTS: SUCROSE; LACTOSE

DRUG FACTS: Active Ingredients

Artemisia vulgaris 6C HPUS, Cuprum metallicum 200C HPUS

Inactive Ingredients

Sucrose, Lactose

Purpose

Helps improve epileptic disorders

Uses

Helps improve epileptic disorders

Warnings

If pregnant or breast feeding ask a health professional before use.

Keep out of reach of children. In case of overdose, get medical help or contact a Poison Control Center (1-800-222-1222) right away.

Direction

Adult or child: Take three pills daily. Leaving a gap of 30 minutes after any food or as advised by your physician.

Manufactured by

Paramesh Banerji Life Sciences, LLC.

North Brunswick, NJ 08902, USA.

Tel: +1-732-743-5936

Email: info@pblifesciences.com

Principal Display Panel

NDC: 69152-0524-1

Alartem 40

Number 524

Homeopathic Medicine

Helps improve epileptic disorders

96 Pills (Approx.)

Product of USA